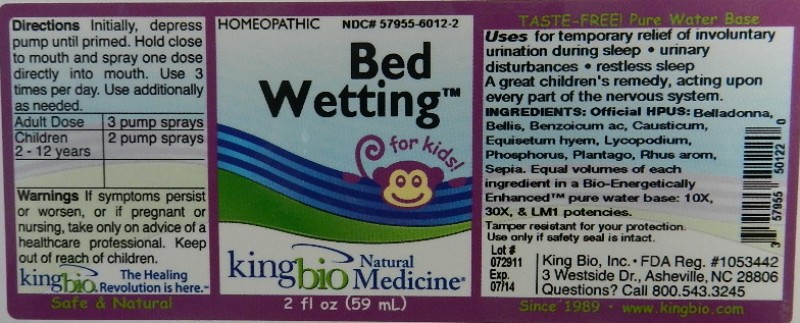 DRUG LABEL: Bed Wetting
NDC: 57955-6012 | Form: LIQUID
Manufacturer: King Bio Inc.
Category: homeopathic | Type: HUMAN OTC DRUG LABEL
Date: 20111223

ACTIVE INGREDIENTS: ATROPA BELLADONNA 10 [hp_X]/59 mL; BELLIS PERENNIS 10 [hp_X]/59 mL; BENZOIC ACID 10 [hp_X]/59 mL; CAUSTICUM 10 [hp_X]/59 mL; EQUISETUM HYEMALE 10 [hp_X]/59 mL; LYCOPODIUM CLAVATUM SPORE 10 [hp_X]/59 mL; PHOSPHORUS 10 [hp_X]/59 mL; PLANTAGO MAJOR 10 [hp_X]/59 mL; RHUS AROMATICA ROOT BARK 10 [hp_X]/59 mL; SEPIA OFFICINALIS JUICE 10 [hp_X]/59 mL
INACTIVE INGREDIENTS: WATER

Bed Wetting

Active Ingredients

Official HPUS: Belladonna, Bellis perennis, Benzoicum acidum, Causticum, Equisetum hyemale, Lycopodium clavatum, Phosphorus, Plantago major, Rhus aromatica, and Sepia.

Reference image bed wetting.jpg

Inactive Ingredient

Equal volumes of each ingredient in a Bio-Energetically Enhanced pure water base: 10X, 30X, and LM1 potencies.

Reference image bed wetting.jpg

Dosage and Administration

Directions: Initially, depress pump until primed. Hold close to mouth and spray one dose directly into mouth. Use 3 times per day. Use additionally as needed.

Adult Dose 3 pump sprays

Children (2-12 years) 2 pump sprays

Reference image bed wetting.jpg

Purpose

Uses for temporary relief of involuntary urination during sleep

- Urinary disturbances
- restless sleep

A great children's remedy, acting upon every part of the nervous system.

Warnings

If symptoms persist or worsen, or if pregnant or nursing, take only on advice of a healthcare professional. Keep out of reach of children.

Other: Tamper resistant for your protection. Use only if safety seal is intact.

Reference image bed wetting.jpg

Keep out of reach of children.

Reference image bed wetting.jpg

Indications and Usage

Uses for temporary relief of involuntary urination during sleep, Urinary disturbances, restless sleep. A great children's remedy, acting upon every part of the nervous system.

Reference image bed wetting.jpg

PACKAGE LABEL

King Bio Inc.

3 Westside Drive

Asheville, NC 28806

Questions? Call 800.543.3245

www.kingbio.com

Sade and Natural

Homeopathic